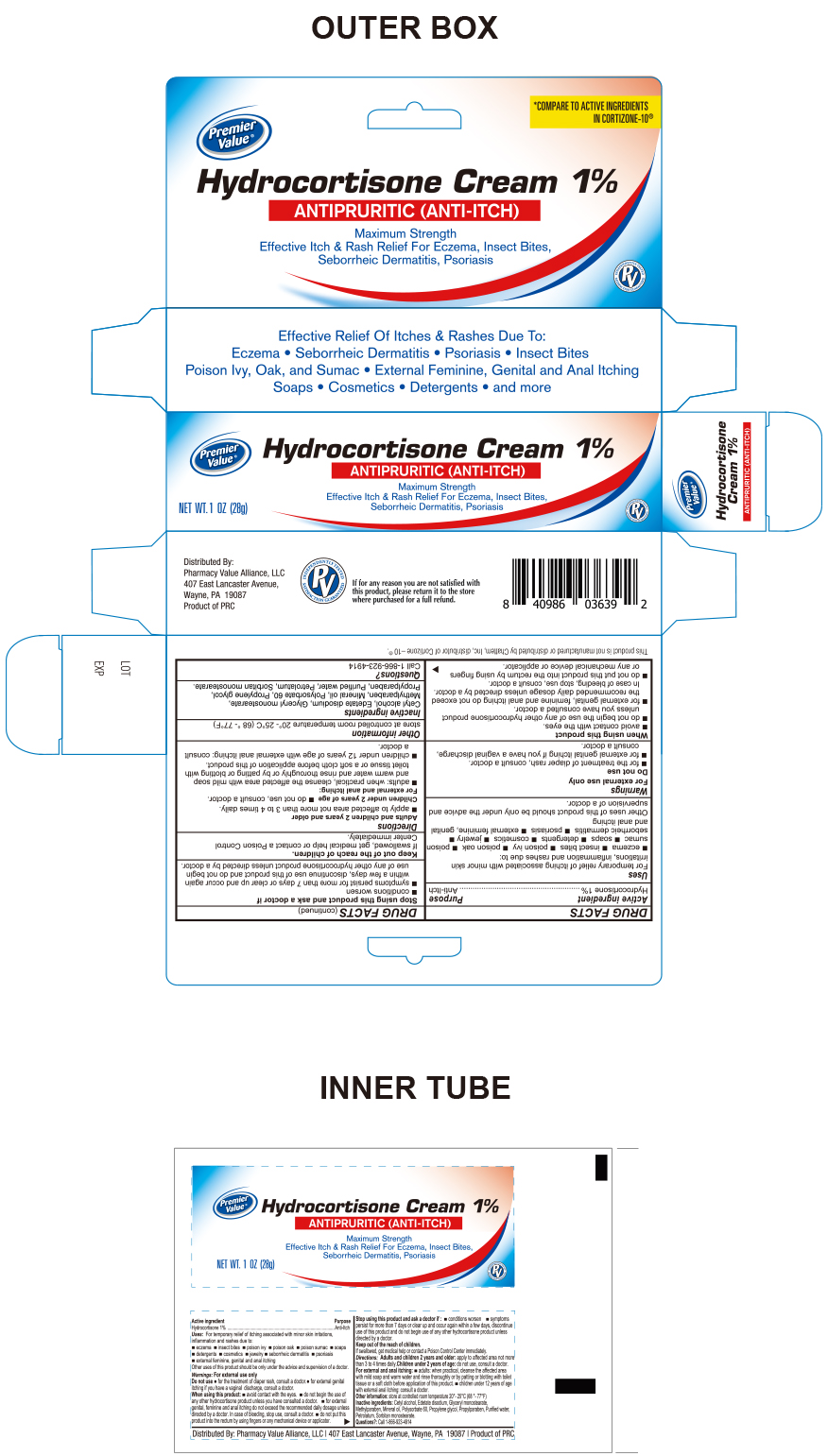 DRUG LABEL: Hydrocortisone
NDC: 68016-149 | Form: CREAM
Manufacturer: Pharmacy Value Alliance LLC
Category: otc | Type: HUMAN OTC DRUG LABEL
Date: 20241220

ACTIVE INGREDIENTS: HYDROCORTISONE 1 g/100 g
INACTIVE INGREDIENTS: POLYSORBATE 60; PROPYLENE GLYCOL; PROPYLPARABEN; SORBITAN MONOSTEARATE; MINERAL OIL; PETROLATUM; WATER; METHYLPARABEN; EDETATE DISODIUM; CETYL ALCOHOL; GLYCERYL MONOSTEARATE

Premier Value Hydrocortisone Cream 1%

Active Ingredient

Hydrocortisone 1%

Purpose

Anti-itch

Keep out of Reach of Children

If Swallowed, get medical help or contact a Poison Control Center Immediately.

Uses

For temporary relief of itching associated with minor skin irritataions, inflammation and rashes due to

- Eczema
- Insect bites
- poison ivy
- poison oak
- poison sumac
- soaps
- detergents
- cosmetics
- jewelry
- seborrheic dermatitis
- psoriasis
- external feminine, genital and anal itching

Other uses of this product should be only under the advice and supervision of a doctor

Warnings

For External Use Only

Do not use

- For the treatment of diaper rash, consult a doctor
- For external genital itching, if you have a vaginal discharge, consult a doctor

When using this Product

- Avoid contact with the eyes.
- Do not begin the use of any other hydrocortisone product unless you have consulted a doctor.
- For external genital, feminine and anal itching do not exceed the recommended daily dosage unless directed by a doctor. In case of bleeding, stop use, consult a doctor
- Do not put this product into the rectum by using fingers or any mechanical device or applicator.

Stop Using this product and ask a doctor if

- Conditions worsen
- Symptoms persist for more than 7 days or clear up and occur again within a few days, discontinue use of this product and do not begin use of any other hydrocortisone product unless directed by a doctor.

Directions

Adults and children 2 years and older

- Apply to affected area not mroe than 3 to 4 times daily.

Children under 2 years of age

- Do not use
- Consult a doctor

For External and Anal Itching

- Adults: When practical, cleanse the affected area with mild soap and warm water and rinse thoroughly or by patting or blotting with toilet tissue or a soft cloth before application of this product.
- Children under 12 years of age with external anal itching; consult a doctor.

Other Information

Store at controlled room temperature 20°-25°C (68°-77°F)

Inactive Ingredients

Cetyl alcohol, Edetate disodium, Glyceryl monostearate, Methylparaben, Mineral oil, Polysorbate 60, Propylene glycol, Propylparaben, Purified Water, Petrolatum, Sorbitan monostearate

Questions

Call 1-866-923-4914

If for any reason you are not satisfied with this product, please return it to the store where purchased for a full refund.

Other Information

This product is not manufactured or distributed by Chattem Inc. distributor of Cortizone -10® Aloe

Distributed By:

Pharmacy Value Alliance, LLC.

407 East Lancaster Avenue

Wayne, PA. 19087

Product of PRC